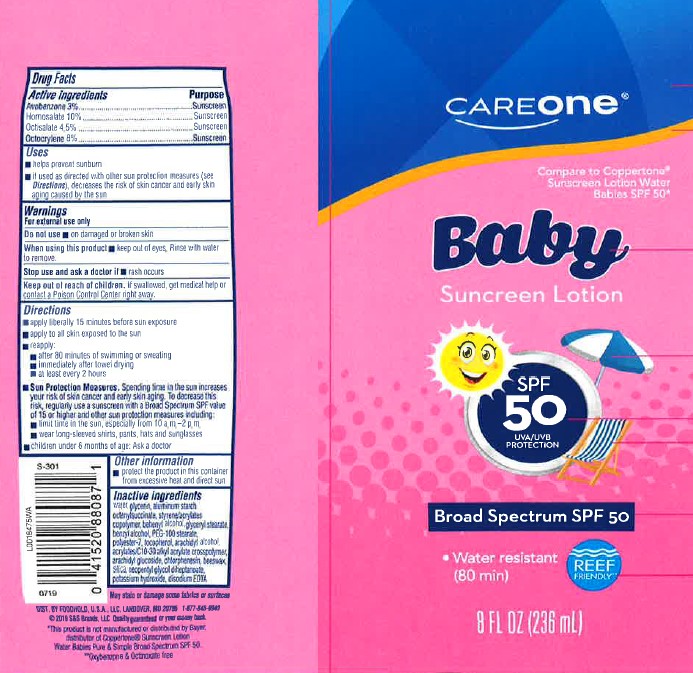 DRUG LABEL: Avobenzone, Homosalate, Octisalate, Octocrylene
NDC: 72476-950 | Form: LOTION
Manufacturer: Retail Business Services, LLC 
Category: otc | Type: HUMAN OTC DRUG LABEL
Date: 20260206

ACTIVE INGREDIENTS: AVOBENZONE 30 mg/1 mL; HOMOSALATE 100 mg/1 mL; OCTISALATE 45 mg/1 mL; OCTOCRYLENE 80 mg/1 mL
INACTIVE INGREDIENTS: WATER; GLYCERIN; ALUMINUM STARCH OCTENYLSUCCINATE; STYRENE/ACRYLAMIDE COPOLYMER (500000 MW); DOCOSANOL; GLYCERYL MONOSTEARATE; BENZYL ALCOHOL; PEG-100 STEARATE; POLYESTER-7; TOCOPHEROL; ARACHIDYL ALCOHOL; CARBOMER INTERPOLYMER TYPE A (ALLYL SUCROSE CROSSLINKED); ARACHIDYL GLUCOSIDE; CHLORPHENESIN; YELLOW WAX; SILICON DIOXIDE; NEOPENTYL GLYCOL DIHEPTANOATE; POTASSIUM HYDROXIDE; EDETATE DISODIUM ANHYDROUS

Care One 950.000/950AA
Sunscreen for Babies SPF 50

Active ingredients

Avobenzone 3%

Homosalate 10%

Octisalate 4.5%

Octocrylene 8%

Purpose

Sunscreen

Uses

- helps prevent sunburn
- if used as directed with other sun protection measures (See Directions), decreases the rist of skin cancer and early skin aging caused by the sun

Warnings

For external use only

Do not use

- on damaged or broken skin

Stop use and ask a doctor if

- rash occurs

Keep out of reach of children.

If swallowed, get medical help or contact a Poison Control Center right away.

Directions

- apply liberaly 15 minutes before sun exposure
- apply to all skin exposed to the sun
- reapply:
- after 80 minutes of swimming or sweating
- immediately after towel drying
- at least every 2 hours
- Sun Protection Measures. Spending time in the sun increases your risk of skin cancer and early skin aging. To decrease this risk, regularly use a sunscreen with Broad Spectrum SPF value of 15 or higher and other sun protection measures including:
- limit time in the sun, especialy from 10 a.m. -2 p.m.
- wear long-sleeved shirts, pants, hats and sunglasses
- children under 6 months of age: Ask a doctor

Other information

- protect the product in this container from excessive heat and direct sun

Inactive ingredients

water, glycerin, aluminum starch octenylsuccinate, styrene/acrylates copolymer, behenyl alcohol, glyceryl stearate, benzyl alcohol, PEG-100 stearate, polyester-7, tocopherol, arachidyl alcohol, acrylates/C10-30 alkyl acrylate crosspolymer, arachidyl glucoside, chlorphenesin, beeswax, silica, neopentyl glycol diheptanoate, potassium hydroxide, disodium EDTA

ADVERSE REACTION

May stain or damage some fabrics or surfaces

Dist by Foodhold USA, LLC Landover, MD 20733 1877-846-9949

(c)2019 S&S Brands, LLC Quality guaranteed or your money back

*This product is not manufactured or distributed by Bayer, distributor of Coppertone Sunscreen Lotion Water Babies Pure & Simple Broad spectrum SPF 50

**Oxybenzone & Octinoxate free

Principal display panel

CareOne

Compare to Coppertone Sunscreen Lotion Water Babies SPF 50*

Baby

Sunscreen Lotion

SPF 50

UVA/UVB protection

Broad Spectrum SPF 50

- Water resistant (80 minutes)

Reef friendly**

8 FL OZ (236 mL)